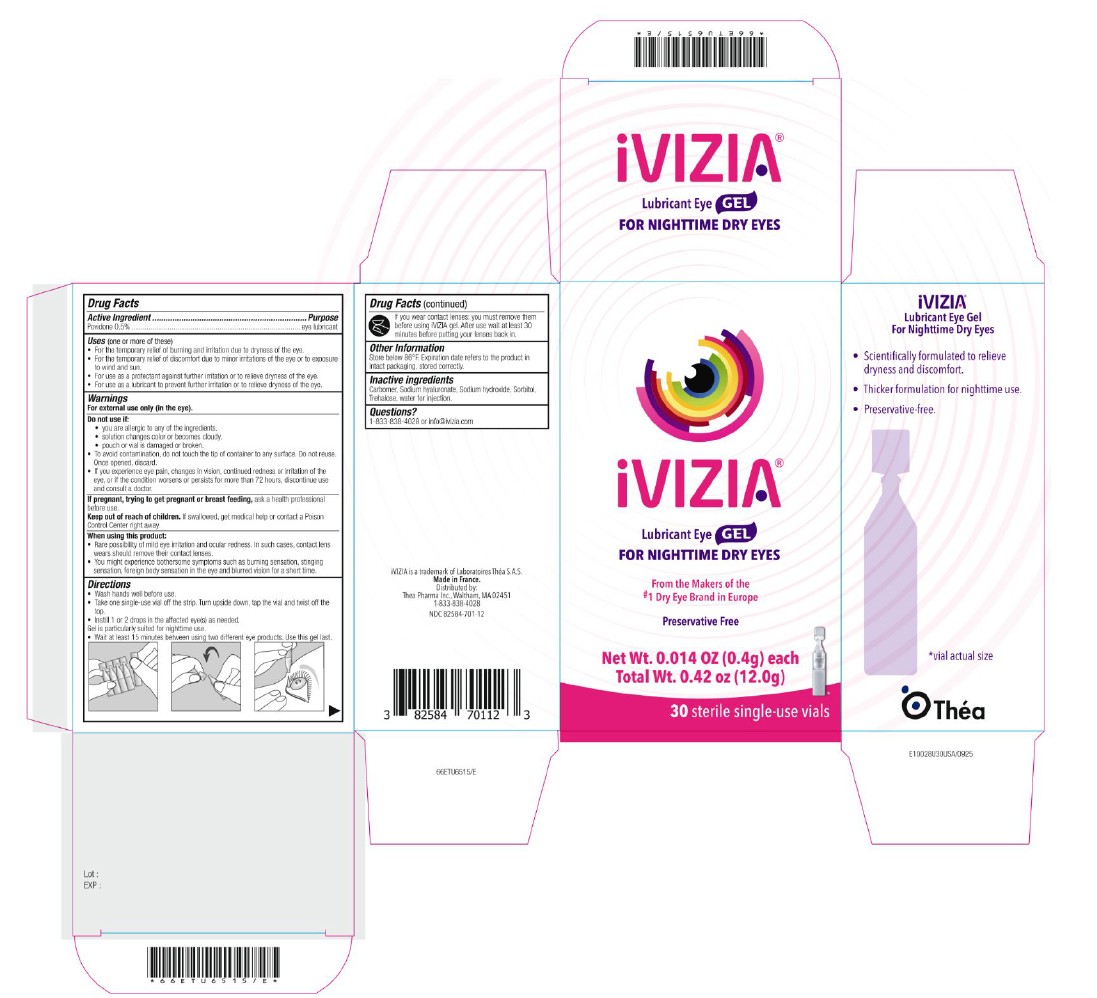 DRUG LABEL: iVIZIA Lubricant Eye Gel
NDC: 82584-701 | Form: GEL
Manufacturer: Thea Pharma Inc.
Category: otc | Type: HUMAN OTC DRUG LABEL
Date: 20260211

ACTIVE INGREDIENTS: POVIDONE, UNSPECIFIED 2.5 mg/0.5 g
INACTIVE INGREDIENTS: SORBITOL; SODIUM HYDROXIDE; TREHALOSE; WATER; HYALURONATE SODIUM; CARBOMER HOMOPOLYMER, UNSPECIFIED TYPE

iVIZIA Lubricant Eye Gel for Nighttime Dry Eyes

Active Ingredient

Povidone 0.5%

Purpose

Eye lubricant

Uses

(one or more of these)

For the temporary relief of burning and irritation due to dryness of the eye
For the temporary relief of discomfort due to minor irritations of the eye or to exposure to wind and sun
For use as a protectant against further irritation or to relieve dryness of the eye
For use as a lubricant to prevent further irritation or to relieve dryness of the eye.

Warnings:

For external use only (in the eye)

Do not use if:
• you are allergic to any of the ingredients.
• solution changes color or becomes cloudy.
• pouch or vial is damaged or broken
• To avoid contamination, do not touch the tip of container to any surface. Do not reuse. Once opened, discard.
• If you experience eye pain, changes in vision, continued redness or irritation of the eye, or if the condition worsens or persists for more than 72 hours, discontinue use and consult a doctor.

PREGNANCY OR BREAST FEEDING

If pregnant, trying to get pregnant or breast feeding, ask a health professional before use.

Keep out of reach of children. If swallowed, get medical help or contact a Poison Control Center right away.

When using this product:
• Rare possibility of mild eye irritation and ocular redness. In such cases, contact lens wears should remove their contact lenses.
• You might experience bothersome symptoms such as burning sensation, stinging sensation, foreign body sensation in the eye and blurred vision for a short time.

Directions

• Wash hands well before use.
• Take one single-use vial off the strip. Turn upside down, tap the vial and twist off the top.
• Instill 1 or 2 drops in the affected eye(s) as needed. Gel is particularly suited for severe dry eye or nighttime use.
• Wait at least 15 minutes between using two different eye products. Use this gel last.

If you wear contact lenses: you must remove them before using iVIZIA gel. After use wait at least 30 minutes before putting your lenses back in.

Other Information

Store below 86°F. Expiration date refers to the product in intact packaging, stored correctly.

Inactive ingredients

Carbomer, Purified water, Sodium hyaluronate, Sodium hydroxide, Sorbitol, Trehalose

Questions?

1-833-838-4028 or info@ivizia.com

Principle Display Panel

iVizia
Lubricant Eye Gel
For Nighttime Dry Eyes
0.014 OZ (0.4g) each

30 sterile single-use vials